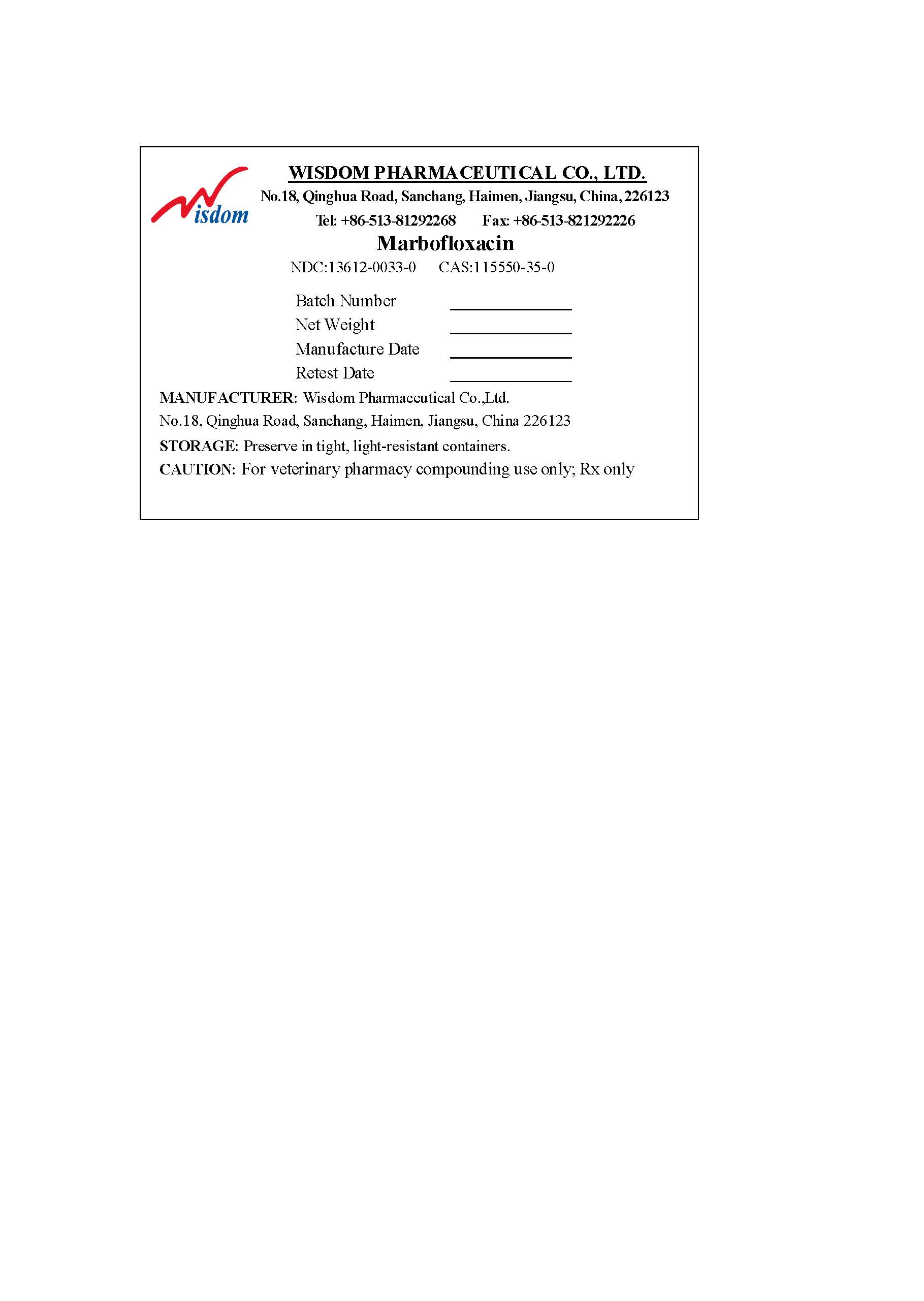 DRUG LABEL: Marbofloxacin
NDC: 13612-0033 | Form: POWDER
Manufacturer: Wisdom Pharmaceutical Co.,Ltd
Category: other | Type: BULK INGREDIENT - ANIMAL DRUG
Date: 20251126

ACTIVE INGREDIENTS: Marbofloxacin 1 kg/1 kg

Marbofloxacin